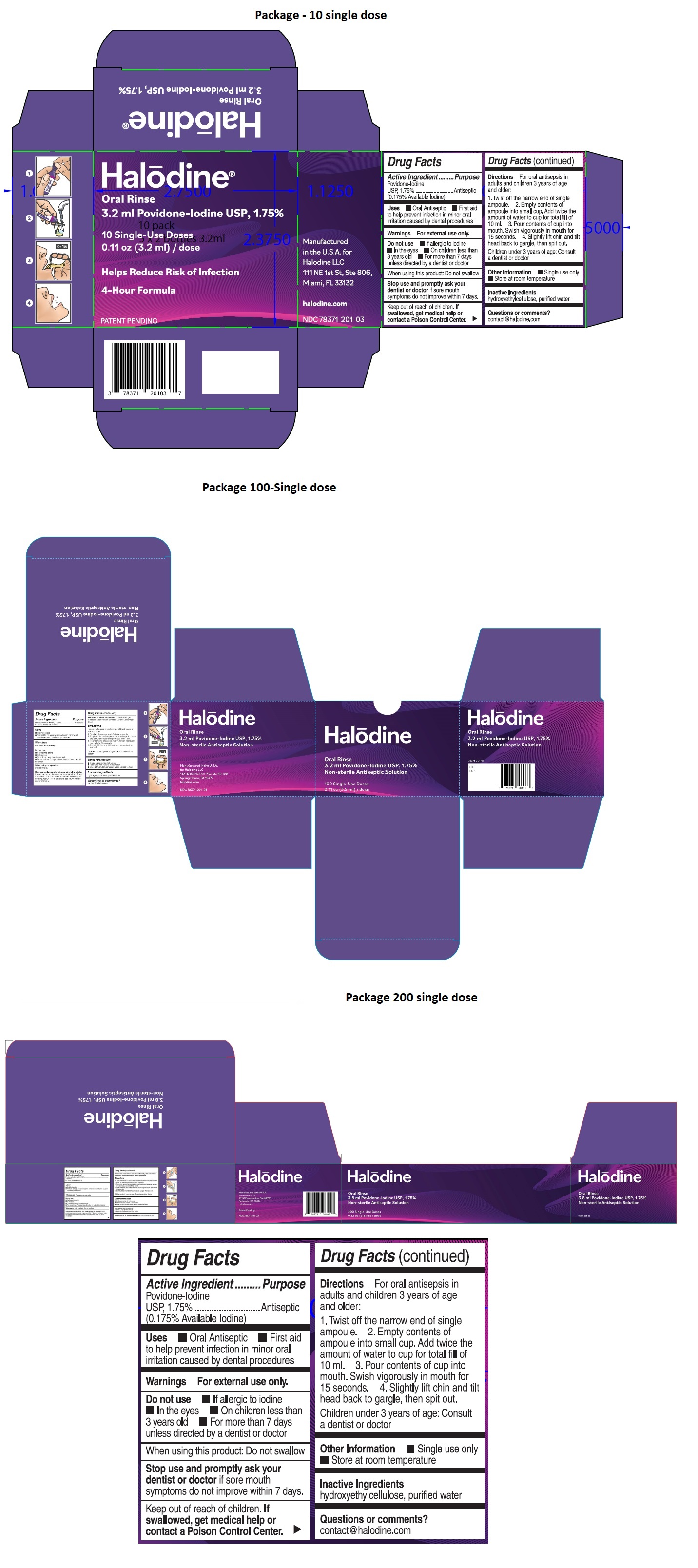 DRUG LABEL: Halodine Oral Rinse
NDC: 78371-201 | Form: SOLUTION
Manufacturer: Halodine LLC
Category: otc | Type: HUMAN OTC DRUG LABEL
Date: 20201113

ACTIVE INGREDIENTS: POVIDONE-IODINE 1.75 mg/1 mL
INACTIVE INGREDIENTS: WATER; HYDROXYETHYL CELLULOSE, UNSPECIFIED

Halodine Oral Rinse

Active Ingredient

Povidone-Iodine USP, 1.75%
(0.175% Available Iodine)

Purpose

Antiseptic

Uses

- Oral Antiseptic
- First aid to help prevent infection in minor oral irritation caused by dental procedures

Warnings

For external use only.

Do not use • If allergic to iodine • In the eyes • On children less than 3 years old • For more than 7 days unless directed by a dentist or doctor

When using this product: Do not swallow

Stop use and promptly ask your dentist or doctor if sore mouth symptoms do not improve within 7 days, if irritation, pain, or redness persists or worsens, or if swelling, rash, or fever develops.

Keep out of reach of children. If swallowed, get medical help or contact a Poison Control Center right away.

Directions

For oral antisepsis in adults and children 3 years of age and older:

1. Twist off the narrow end of single ampoule.
2. Empty contents of ampoule into small cup. Add twice the amount of water to cup for total fill of 10 ml.
3. Pour contents of cup into mouth. Swish vigorously in mouth for 15 seconds.
4. Slightly lift chin and tilt head back to gargle, then spit out.

Children under 3 years of age: Consult a dentist or doctor

Other Information

- Single use only; do not reuse
- Not made with natural rubber latex
- Store at room temperature; avoid excessive heat

Inactive Ingredients

hydroxyethylcellulose, purified water

Questions or comments?

contact@halodine.com

Helps Reduce Risk of Infection

4-Hour Formula

Non-Sterile Antiseptic Solution

PATENT PENDING

Manufactured in the U.S.A. for Halodine LLC

111 NE 1st St, Ste 806, Miami, FL 33132

halodine.com